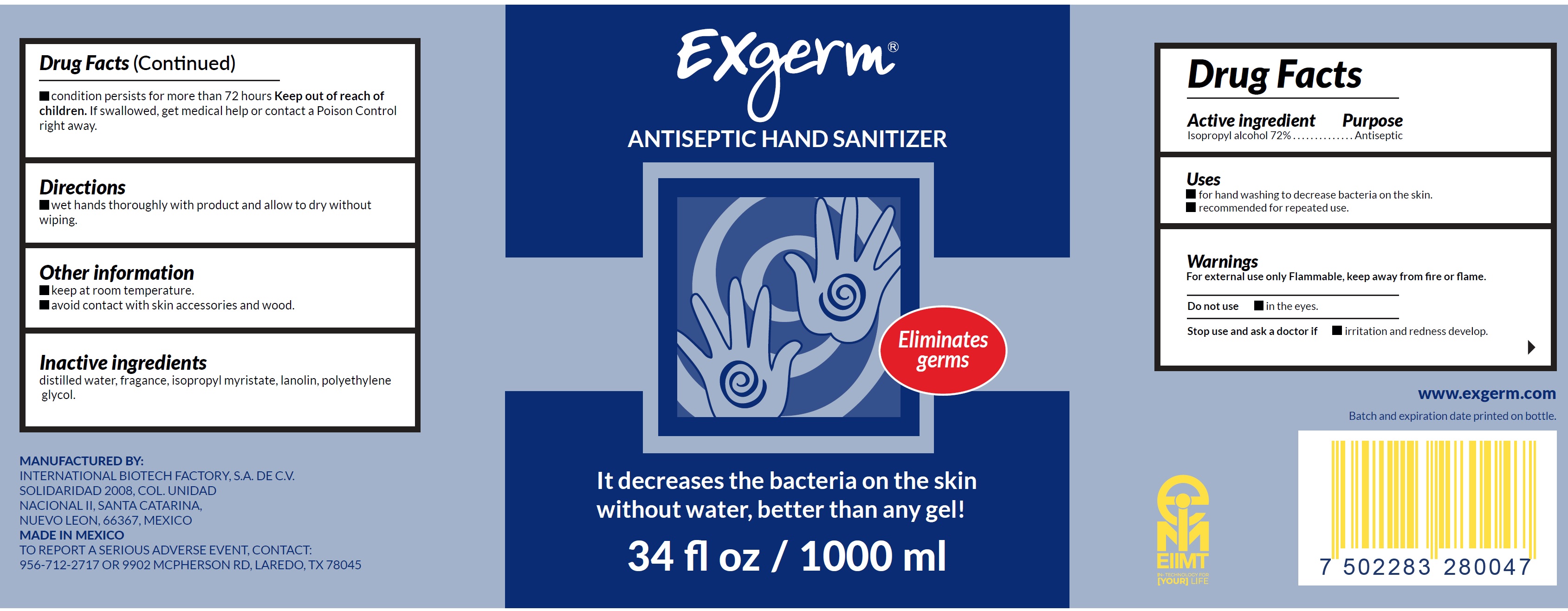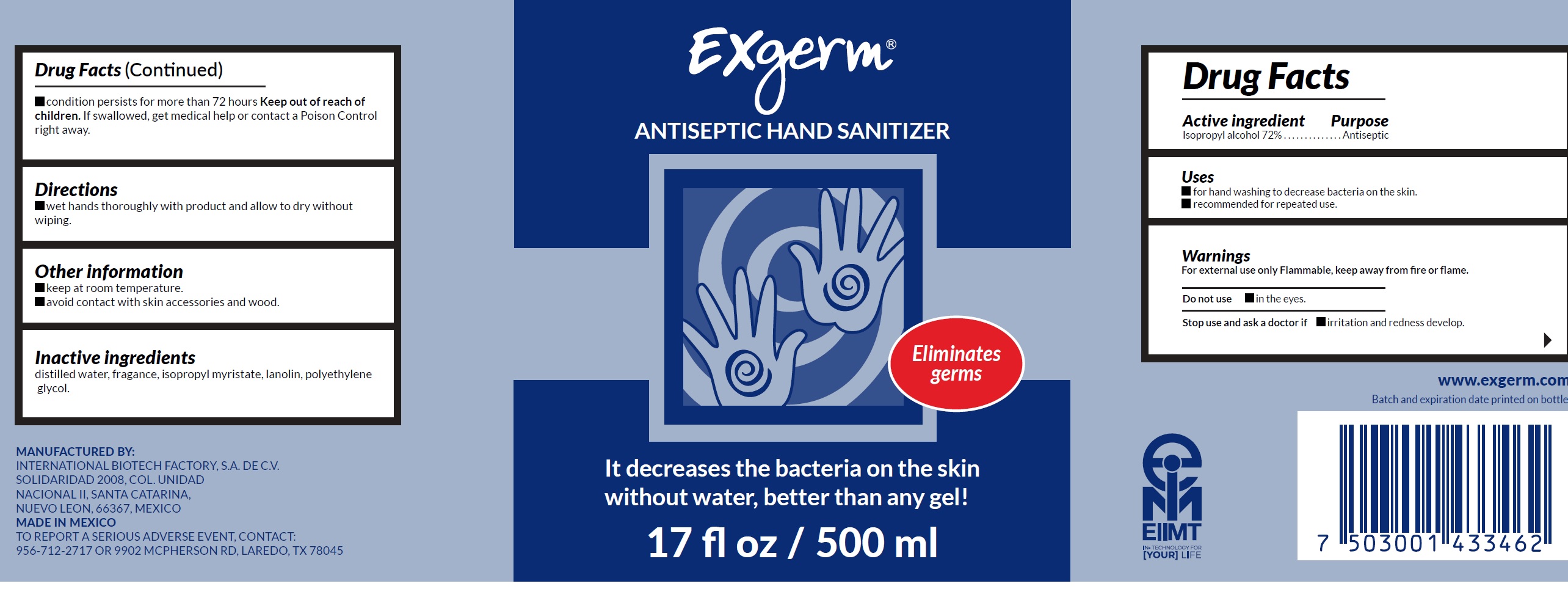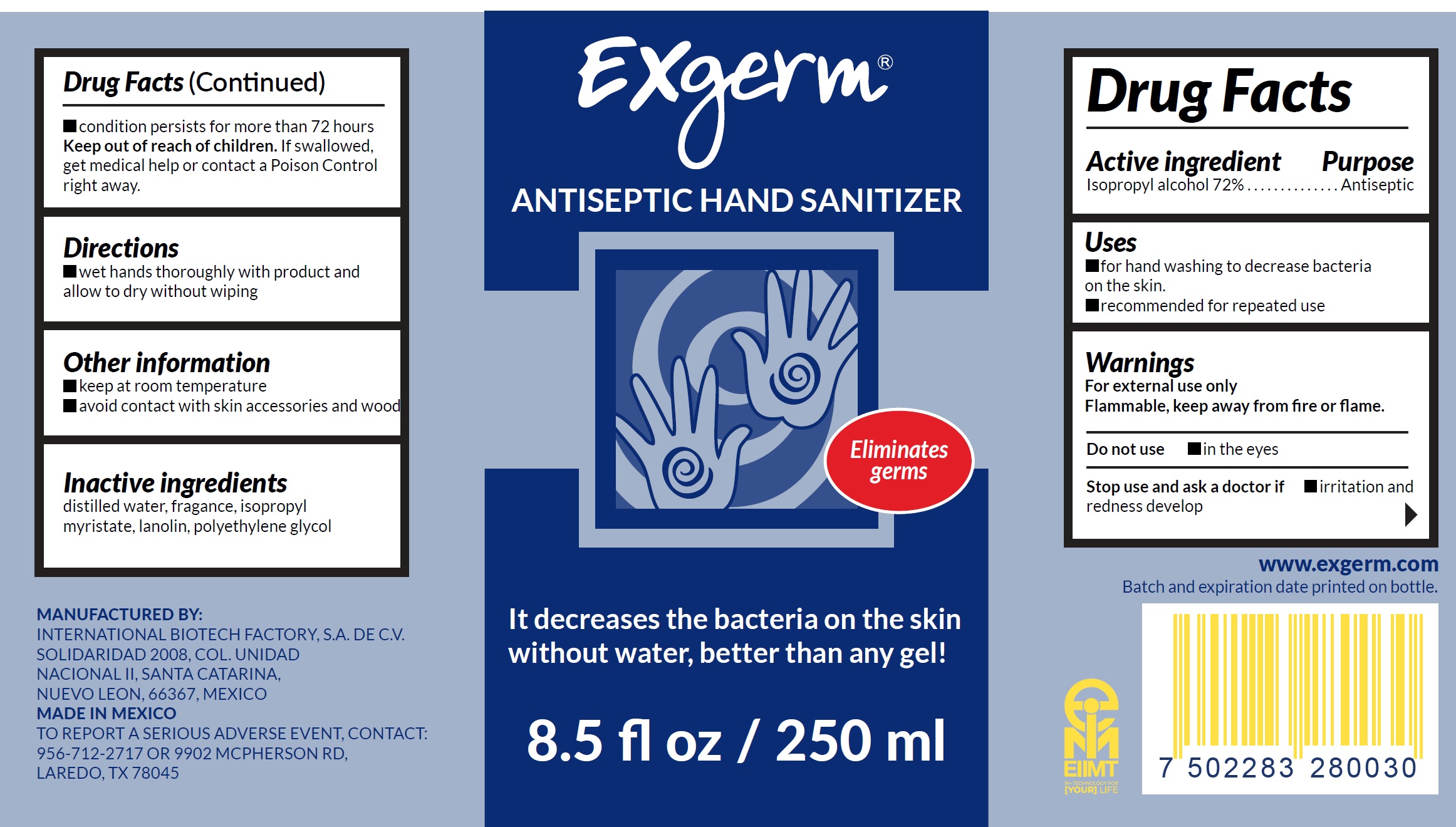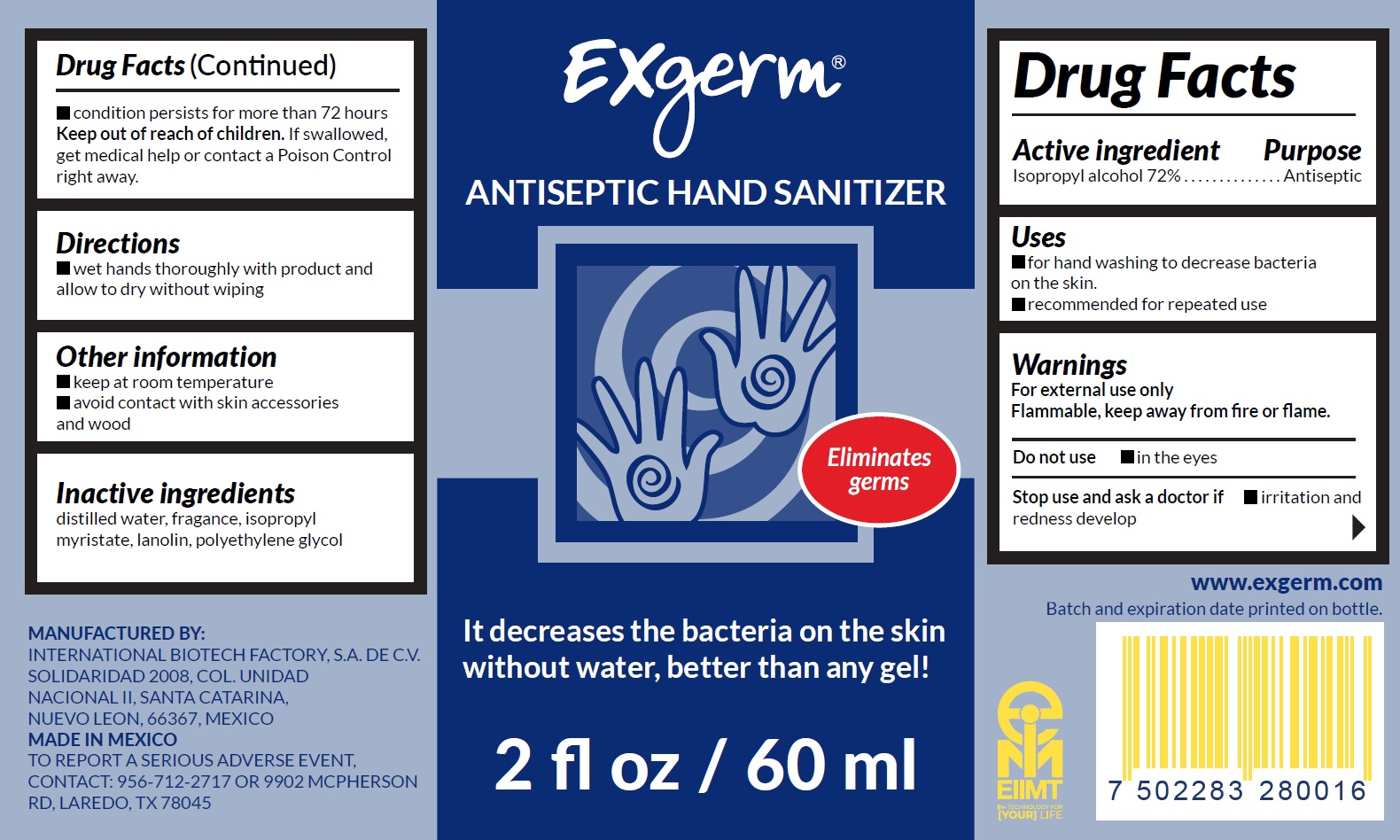 DRUG LABEL: Exgerm Antiseptic Hand Sanitizer
NDC: 80284-000 | Form: LIQUID
Manufacturer: International Biotech Factory, S.A. de C.V.
Category: otc | Type: HUMAN OTC DRUG LABEL
Date: 20231221

ACTIVE INGREDIENTS: ISOPROPYL ALCOHOL 0.72 mL/1 mL
INACTIVE INGREDIENTS: WATER; ISOPROPYL MYRISTATE; LANOLIN; POLYETHYLENE GLYCOL, UNSPECIFIED

Exgerm Antiseptic Hand Sanitizer 72% Isopropyl Alcohol

Active ingredient

Isopropyl alcohol 72%

Purpose

Antiseptic

Uses

- for hand washing to decrease bacteria on the skin.
- recommended for repeated use.

Warnings

For external use only Flammable, keep away from fire or flame.

Do not use

- in the eyes.

Stop use and ask a doctor if

- irritation and redness develop.
- condition persists for more than 72 hours

Keep out of reach of children.

If swallowed, get medical help or contact a Poison Control right away.

Directions

- wet hands thoroughly with product and allow to dry without wiping.

Other information

- keep at room temperature.
- avoid contact with skin accessories and wood.

Inactive ingredients

distilled water, fragance, isopropyl myristate, lanolin, polyethylene glycol.